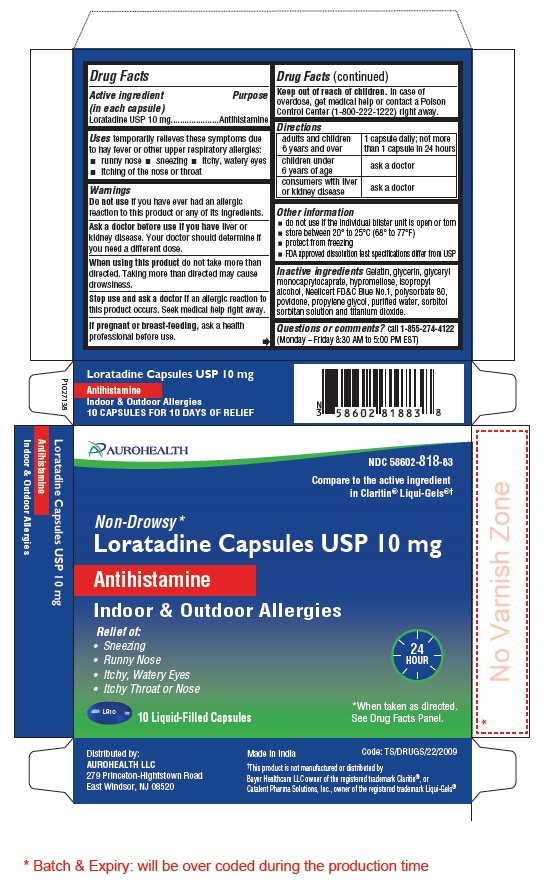 DRUG LABEL: Loratadine
NDC: 58602-818 | Form: CAPSULE, LIQUID FILLED
Manufacturer: Aurohealth LLC
Category: otc | Type: Human OTC Drug Label
Date: 20241023

ACTIVE INGREDIENTS: LORATADINE 10 mg/1 1
INACTIVE INGREDIENTS: GELATIN TYPE B BOVINE (160 BLOOM); GLYCERIN; GLYCERYL MONO- AND DICAPRYLOCAPRATE; HYPROMELLOSE 2910 (3 MPA.S); ISOPROPYL ALCOHOL; FD&C BLUE NO. 1; POLYSORBATE 80; POVIDONE K30; PROPYLENE GLYCOL; WATER; SORBITOL; TITANIUM DIOXIDE

Drug Facts

Active ingredient

(in each capsule)

Loratadine USP 10 mg

Purpose

Antihistamine

Uses

temporarily relieves these symptoms due to hay fever or other upper respiratory allergies:

- runny nose
- sneezing
- itchy, watery eyes
- itching of the nose or throat

Warnings

Do not use if you have ever had an allergic reaction to this product or any of its ingredients.

Ask a doctor before use if you have

liver or kidney disease. Your doctor should determine if you need a different dose.

When using this product

do not take more than directed. Taking more than directed may cause drowsiness.

Stop use and ask a doctor if

an allergic reaction to this product occurs. Seek medical help right away.

If pregnant or breast-feeding,

ask a health professional before use.

Keep out of reach of children.

In case of overdose, get medical help or contact a Poison Control Center (1-800-222-1222) right away.

Directions

adults and children 6 years and over | 1 capsule daily; not more than 1 capsule in 24 hours
children under 6 years of age | ask a doctor
consumers with liver or kidney disease | ask a doctor

Other information

- do not use if the individual blister unit is open or torn
- store between 20° to 25°C (68° to 77°F)
- protect from freezing
- FDA approved dissolution test specifications differ from USP

Inactive ingredients

Gelatin, glycerin, glyceryl monocaprylocaprate, hypromellose, isopropyl alcohol, Neelicert FD&C Blue No.1, polysorbate 80, povidone, propylene glycol, purified water, sorbitol sorbitan solution and titanium dioxide.

Questions or comments?

call 1-855-274-4122 (Monday – Friday 8:30 AM to 5:00 PM EST)
Distributed by:
AUROHEALTH LLC
279 Princeton-Hightstown Road
East Windsor, NJ 08520
Made in India
Code: TS/DRUGS/22/2009

PACKAGE LABEL-PRINCIPAL DISPLAY PANEL - 10 mg (10 Capsule Blister Carton)

AUROHEALTH

NDC 58602-818-83

Compare to the active ingredient

in Claritin® Liqui-Gels®†

Non-Drowsy*

Loratadine Capsules USP 10 mg

Antihistamine

Indoor & Outdoor Allergies

Relief of:

- Sneezing
- Runny Nose
- Itchy, Watery Eyes
- Itchy Throat or Nose

24 HOUR

10 Liquid-Filled Capsules

*When taken as directed.

See Drug Facts Panel.